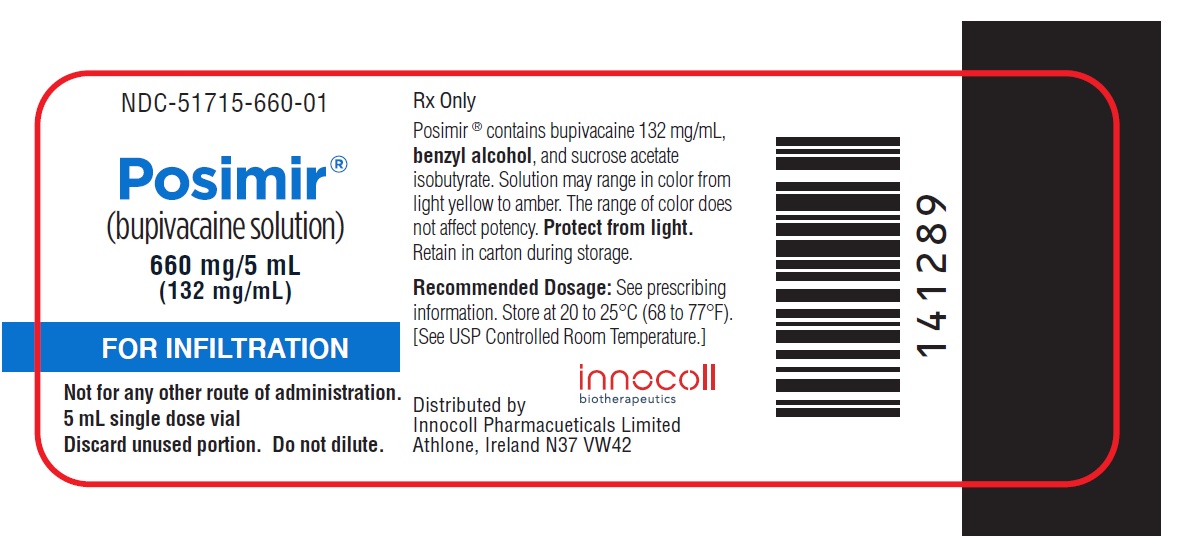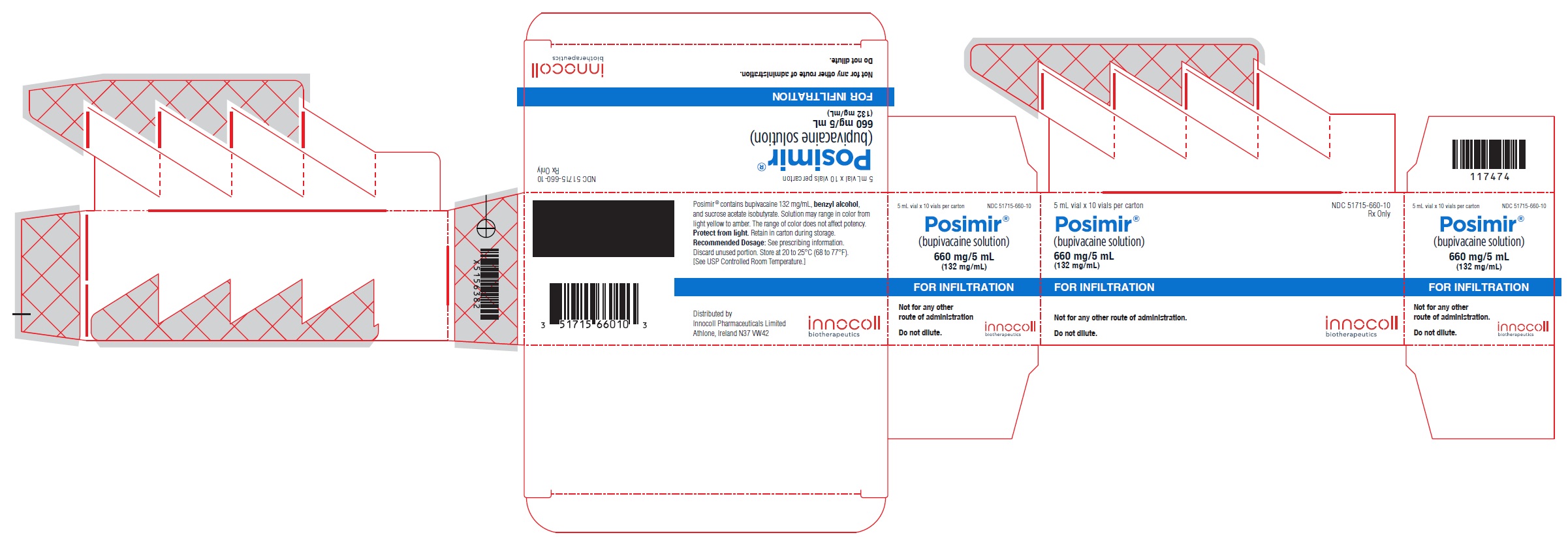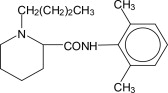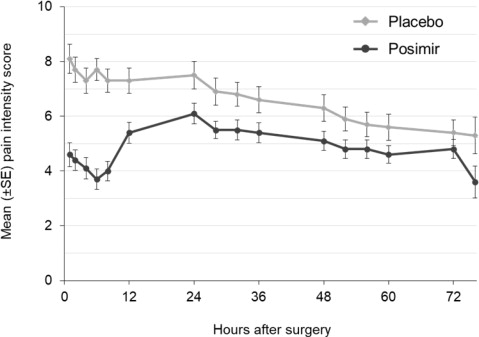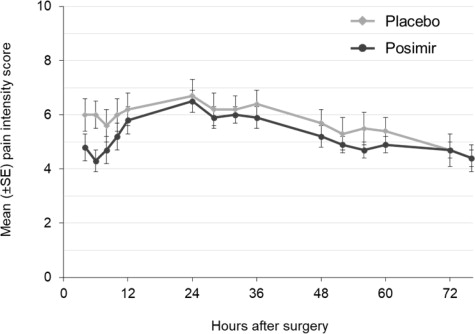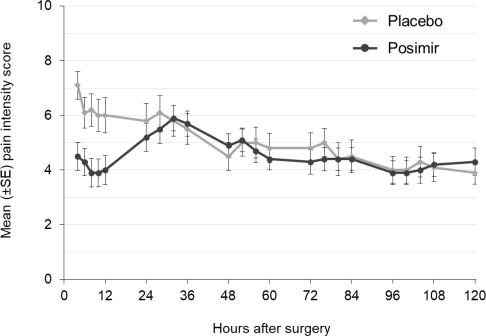 DRUG LABEL: POSIMIR
NDC: 51715-660 | Form: SOLUTION
Manufacturer: INNOCOLL PHARMACEUTICALS
Category: prescription | Type: HUMAN PRESCRIPTION DRUG LABEL
Date: 20221212

ACTIVE INGREDIENTS: BUPIVACAINE 660 mg/5 mL
INACTIVE INGREDIENTS: BENZYL ALCOHOL; SUCROSE ACETATE ISOBUTYRATE

HIGHLIGHTS OF PRESCRIBING INFORMATION

These highlights do not include all the information needed to use POSIMIR® safely and effectively. See full prescribing information for POSIMIR.
POSIMIR (bupivacaine solution) for infiltration use
Initial U.S. Approval: 1972

WARNING: RISK OF POTENTIAL ADVERSE EMBOLIC EFFECTS RESULTING FROM INADVERTENT INTRAVASCAULAR INJECTION

WARNING: RISK OF POTENTIAL ADVERSE EMBOLIC EFFECTS RESULTING FROM INADVERTENT INTRAVASCULAR INJECTION

See full prescribing information for complete boxed warning.

Inadvertent intravascular injection could cause POSIMIR droplets to be deposited in the pulmonary and other capillary beds. Administer POSIMIR into the subacromial space at the end of arthroscopic shoulder surgery. Direct arthroscopic visualization must be used to confirm proper placement of the needle tip before injecting POSIMIR. (5.1)

1 INDICATIONS AND USAGE

POSIMIR contains an amide local anesthetic and is indicated in adults for administration into the subacromial space under direct arthroscopic visualization to produce post-surgical analgesia for up to 72 hours following arthroscopic subacromial decompression.

Limitations of Use

Safety and effectiveness have not been established in other surgical procedures, including soft tissue surgical procedures, other orthopedic procedures, including for intra-articular administration, and boney procedures, or when used for neuraxial or peripheral nerve blockade.

2 DOSAGE AND ADMINISTRATION

- For single-dose administration only. (2.1)
- Do not dilute or mix with local anesthetics or other drugs or diluents.
- . (2.1)
- Do not convert from other bupivacaine formulations to POSIMIR. Do not substitute. (2.1)
- Avoid additional use of local anesthetics within 168 hours following administration of POSIMIR.
- The recommended dose is 660 mg (5 mL). (2.2).

See Full Prescribing Information for additional dosage and administration instructions and compatibility considerations. (2.3, 2.4)

3 DOSAGE FORMS AND STRENGTHS

Solution: 5 mL single-dose vial, 660 mg/5 mL (132 mg/mL) (3).

4 CONTRAINDICATIONS

- Patients with a known hypersensitivity (e.g. anaphylactic reactions and serious skin reactions) to any amide local anesthetic, or other components of POSIMIR.
- Patients undergoing obstetrical paracervical block anesthesia (4).

5 WARNINGS AND PRECAUTIONS

- Risk of Joint Cartilage Necrosis with Unapproved Intra-articular Use: A study evaluating the effects of POSIMIR and POSIMIR vehicle in dogs following an intra-articular administration demonstrated joint cartilage necrosis (5.2, 13.2).
- Risk of Systemic Toxicity: Careful and constant monitoring of cardiovascular and respiratory (adequacy of ventilation) vital signs and the patient's state of consciousness should be performed after injection of bupivacaine. (5.3)
- Methemoglobinemia: Cases of methemoglobinemia have been reported in association with local anesthetic use. See Full Prescribing Information for more detail on managing these risks. (5.4)
- Chondrolysis with Intra-Articular Infusion: Intra-articular infusions of local anesthetics including POSIMIR following arthroscopic and other surgical procedures is an unapproved use, and there have been post-marketing reports of chondrolysis in patients receiving such infusions. (5.5)

6 ADVERSE REACTIONS

Adverse reactions reported with an incidence greater than or equal to 10% and greater than control following POSIMIR administration in shoulder surgery were dizziness, dysgeusia, dysuria, headache, hypoesthesia, paresthesia, tinnitus, and vomiting (6.1).

Adverse reactions reported with an incidence greater than or equal to 10% and greater than control following POSIMIR administration in soft tissue surgical procedures were anemia, bradycardia, constipation, C-reactive protein increased, diarrhea, dizziness, dysgeusia, headache, nausea, post procedural contusion (bruising), procedural pain, pruritus, pyrexia, somnolence, surgical site bleeding, visible bruising, and vomiting (6.1).

To report SUSPECTED ADVERSE REACTIONS, contact Innocoll at 1-833-606-1421 or FDA at 1-800-FDA-1088 or www.fda.gov/medwatch.

8 USE IN SPECIFIC POPULATIONS

Moderate to Severe Hepatic Impairment: Consider reduced dosing and increased monitoring for bupivacaine toxicity. (8.6)

FULL PRESCRIBING INFORMATION

WARNING: RISK OF POTENTIAL ADVERSE EMBOLIC EFFECTS RESULTING FROM INADVERTENT INTRAVASCAULAR INJECTION

Inadvertent intravascular injection could cause POSIMIR droplets to be deposited in the pulmonary and other capillary beds. Administer POSIMIR into the subacromial space at the end of arthroscopic shoulder surgery. Direct arthroscopic visualization must be used to confirm proper placement of the needle tip before injecting POSIMIR. [see Warnings and Precautions (5.1)] .

1 INDICATIONS AND USAGE

POSIMIR is indicated in adults for administration into the subacromial space under direct arthroscopic visualization to produce post-surgical analgesia for up to 72 hours following arthroscopic subacromial decompression.

Limitations of Use

Safety and effectiveness have not been established in other surgical procedures, including soft tissue surgical procedures, other orthopedic procedures, including for intra-articular administration, and boney procedures, or when used for neuraxial or peripheral nerve blockade.

2 DOSAGE AND ADMINISTRATION

2.1 Important Dosage and Administration Information

- POSIMIR is intended for single-dose administration only.
- Do not dilute or mix POSIMIR with local anesthetics or other drugs or diluents.
- As there is a potential risk of severe, life-threatening adverse reactions associated with the administration of bupivacaine, POSIMIR should be administered in a setting where trained personnel and equipment are available to promptly treat patients who show evidence of neurological or cardiac toxicity.
- Different formulations of bupivacaine are not bioequivalent to POSIMIR even if the milligram dosage is the same. It is not possible to convert dosing from any other formulations of bupivacaine to POSIMIR and vice versa. Do not substitute.
- The toxic effects of local anesthetics are additive. Avoid additional use of local anesthetics within 168 hours following administration of POSIMIR.
- Avoid intravascular administration of POSIMIR. Convulsions and cardiac arrest have occurred following accidental intravascular injection of bupivacaine and other amide-containing products.
- POSIMIR is not indicated for the following routes of administration.
  - Epidural
  - Intrathecal
  - Intravascular
  - Intra-articular use [see Nonclinical Toxicology (13.2)]
  - Regional nerve blocks
  - Pre-incisional or pre-procedural locoregional anesthetic techniques that require deep and complete sensory block in the area of administration.

2.2 Recommended Dose

The recommended dose of POSIMIR is 660 mg (5 mL).

2.3 Preparation, Administration, and Dosing Instructions

- POSIMIR is ready to use and does not require dilution or mixing.
- Prior to administration, draw up POSIMIR into a 5 mL syringe using a large bore needle (16 gauge or larger). Once the syringe has been filled, discard the large bore needle.
- At the close of surgery, administer the entire 5 mL dose of POSIMIR into the subacromial space using an 18 gauge or larger-bore needle. The needle may be inserted through an existing arthroscopic port or through intact skin to reach the subacromial space. Confirm correct placement of the needle tip within the subacromial space by direct arthroscopic visualization.
- Do not administer POSIMIR into the glenohumeral intra-articular space.

2.4 Compatibility Considerations

POSIMIR is compatible with:

- Commonly implantable materials, such as polypropylene and polyester
- Silk, nylon, gut, polypropylene, polydioxanone, and polyglycolic acid sutures

3 DOSAGE FORMS AND STRENGTHS

POSIMIR (bupivacaine solution) is a sterile, nonpyrogenic, clear, light yellow to amber solution in a clear, glass vial.

- 5 mL single-dose vial: 660 mg/5 mL (132 mg/mL)

4 CONTRAINDICATIONS

POSIMIR is contraindicated in:

- Patients with a known hypersensitivity (e.g. anaphylactic reactions and serious skin reactions) to any amide local anesthetic, or other components of POSIMIR.
- Patients undergoing obstetrical paracervical block anesthesia. The use of bupivacaine HCl with this technique has resulted in fetal bradycardia and death.

5 WARNINGS AND PRECAUTIONS

5.1 Risk of Potential Adverse Embolic Effects Resulting from Inadvertent Intravascular Injection

Inadvertent intravascular injection could cause POSIMIR droplets to be deposited in the pulmonary and other capillary beds. Administer POSIMIR into the subacromial space at the end of arthroscopic shoulder surgery. Direct arthroscopic visualization must be used to confirm proper placement of the needle tip before injecting POSIMIR.

5.2 Risk of Joint Cartilage Necrosis with Unapproved Intra-articular Use

The safety and effectiveness of POSIMIR in surgical procedures other than subacromial decompression have not been established, and POSIMIR is not approved for use via intra-articular injection. A study evaluating the effects of POSIMIR and POSIMIR vehicle in dogs following an intra-articular administration demonstrated joint cartilage necrosis [ see Nonclinical Toxicology (13.2) ].

5.3 Risk of Systemic Toxicity

Unintended intravascular injection of POSIMIR may be associated with systemic toxicities, including CNS or cardiorespiratory depression and coma, progressing ultimately to respiratory arrest. Direct arthroscopic visualization must be used to confirm proper placement of the needle tip in the subacromial space before injecting POSIMIR.

The safety and effectiveness of bupivacaine depend on proper dosage, correct technique, adequate precautions, and readiness for emergencies. Careful and constant monitoring of cardiovascular and respiratory (adequacy of ventilation) vital signs and the patient's state of consciousness should be performed after injection of bupivacaine.

Possible early warning signs of central nervous system (CNS) toxicity are restlessness, anxiety, incoherent speech, lightheadedness, numbness and tingling of the mouth and lips, metallic taste, tinnitus, dizziness, blurred vision, tremors, twitching, CNS depression, or drowsiness. Delay in proper management of systemic toxicity, underventilation from any cause, and/or altered sensitivity may lead to the development of acidosis, cardiac arrest, and, possibly, death.

Avoid additional use of local anesthetics within 168 hours following administration of POSIMIR. Injection of repeated doses of bupivacaine may cause significant increases in plasma levels due to slow accumulation of the drug or its metabolites, or to slow metabolic degradation. Tolerance to elevated blood levels varies with the status of the patient. Consider increased monitoring for systemic toxicity in debilitated, elderly, or acutely ill patients.

5.4 Methemoglobinemia

Cases of methemoglobinemia have been reported in association with local anesthetic use. Although all patients are at risk for methemoglobinemia, patients with glucose-6-phosphate dehydrogenase deficiency, congenital or idiopathic methemoglobinemia, cardiac or pulmonary compromise, infants under 6 months of age, and concurrent exposure to oxidizing agents or their metabolites are more susceptible to developing clinical manifestations of the condition [ see Drug Interactions (7)]. If local anesthetics must be used in these patients, close monitoring for symptoms and signs of methemoglobinemia is recommended.

Signs of methemoglobinemia may occur immediately or may be delayed some hours after exposure, and are characterized by a cyanotic skin discoloration and/or abnormal coloration of the blood. Methemoglobin levels may continue to rise; therefore, immediate treatment is required to avert more serious central nervous system and cardiovascular adverse effects, including seizures, coma, arrhythmias, and death. Discontinue any oxidizing agents. Depending on the severity of the signs and symptoms, patients may respond to supportive care, i.e., oxygen therapy, hydration. A more severe clinical presentation may require treatment with methylene blue, exchange transfusion, or hyperbaric oxygen.

5.5 Chondrolysis with Intra-Articular Infusion of Local Anesthetics

Intra-articular infusions of local anesthetics including bupivacaine following arthroscopic and other surgical procedures is an unapproved use, and there have been post-marketing reports of chondrolysis in patients receiving such infusions. The majority of reported cases of chondrolysis have involved the shoulder joint; cases of gleno-humeral chondrolysis have been described in pediatric patients and adult patients following intra-articular infusions of local anesthetics with and without epinephrine for periods of 48 to 72 hours. There is insufficient information to determine whether shorter infusion periods are associated with chondrolysis. The time of onset of symptoms, such as joint pain, stiffness, and loss of motion can be variable, but may begin as early as the second month after surgery. Currently, there is no effective treatment for chondrolysis; patients who have experienced chondrolysis have required additional diagnostic and therapeutic procedures and some required arthroplasty or shoulder replacement.

5.6 Risk of Toxicity in Patients with Hepatic Impairment

Because amide local anesthetics such as bupivacaine are metabolized by the liver, consider reduced dosing and increased monitoring for bupivacaine systemic toxicity in patients with moderate to severe hepatic impairment who are treated with POSIMIR [see Use in Specific Populations (8.6) ].

5.7 Risk of Use in Patients with Impaired Cardiovascular Function

Care should be taken when considering the use of POSIMIR in patients with impaired cardiovascular function (e.g., hypotension, heartblock) because they may be less able to compensate for functional changes associated with the prolongation of AV conduction produced by bupivacaine. Consider reduced dosing. Monitor patients closely for blood pressure, heart rate, and ECG changes.

6 ADVERSE REACTIONS

The following adverse reactions to bupivacaine hydrochloride are described in other sections of the prescribing information:

- Systemic Toxicity with Intravascular Injection [see Warnings and Precautions (5.3) ]
- Methemoglobinemia [see Warnings and Precautions (5.4) ]
- Chondrolysis with Intra-Articular Infusion [see Warnings and Precautions (5.5) ]
- Cardiovascular System Reactions [see Warnings and Precautions (5.7) ]

6.1 Clinical Trials Experience

Because clinical trials are conducted under widely varying conditions, adverse reaction rates observed in the clinical trials of a drug cannot be directly compared to rates observed in the clinical trials of another drug and may not reflect the rates observed in practice.

The safety of POSIMIR, doses ranging from 2.5 mL to 5 mL, was evaluated in 10 randomized, double-blind, controlled trials. Overall, POSIMIR 5 mL, the recommended dose, has been administered to a total of 735 patients in clinical trials using a variety of administration methods, including the recommend method of infiltration. Three trials were controlled with bupivacaine HCl, two trials were controlled with bupivacaine HCl and vehicle placebo, and five trials were controlled with vehicle placebo. An additional 47 patients were treated with saline placebo in one of the bupivacaine HCl-controlled trials. The evaluated surgical procedures included inguinal hernia repair, subacromial decompression of the shoulder, abdominal hysterectomy, laparotomy, laparoscopic cholecystectomy, and laparoscopically-assisted colectomy.

Shoulder surgical procedures

There were three studies evaluating the safety of POSIMIR administered during shoulder surgery.

In Study 1, one of three treatments was administered into the subacromial space at the end of surgery: POSIMIR, vehicle placebo, or bupivacaine HCl. Table 1 presents commonly-reported adverse reactions from Study 1.

Table 1. Commonly Reported Adverse Reactions from Study 1 (Incidence ≥ 2% and More Frequent than Bupivacaine HCl or Vehicle Placebo).
Preferred Term, n (%) | Posimir (N=53) | Bupivacaine HCl (n=29) | Vehicle Placebo (N=25)
Headache | 3 (5.7%) | 1 (3.4%) | 1 (4.0%)
Electrocardiogram T wave inversion | 2 (3.8%) | 0 | 0
Hypoesthesia | 2 (3.8%) | 1 (3.4%) | 1 (4.0%)
Pruritus generalized | 2 (3.8%) | 0 | 0

In Study 2 and Study 3, patients were administered either POSIMIR or vehicle placebo into the subacromial space at the end of surgery. Table 2 presents commonly-reported adverse reactions from Studies 2 and 3.

Table 2. Commonly Reported Adverse Reactions Pooled from Study 2 and Study 3 (Incidence ≥ 2% and More Frequent than Vehicle Placebo).
Preferred Term, n (%)* | Posimir (N=75) | Vehicle Placebo (N=44)
Dizziness | 30 (40.3%) | 17 (38.3%)
Vomiting | 22 (29.0%) | 12 (26.6%)
Headache | 17 (23.3%) | 7 (16.3%)
Paresthesia | 14 (18.4%) | 7 (15.4%)
Dysgeusia | 13 (17.6%) | 7 (14.9%)
Hypoesthesia | 13 (17.3%) | 7 (15.8%)
Tinnitus | 10 (13.2%) | 3 (6.7%)
Dysuria | 8 (10.1%) | 4 (10.1%)
Pyrexia | 7 (9.3%) | 2 (4.6%)
Insomnia | 5 (7.1%) | 0
Dyspnea | 3 (3.8%) | 0
Muscle twitching | 3 (3.8%) | 0
Peripheral swelling | 3 (3.9%) | 0
Urinary retention | 2 (2.7%) | 1 (2.1%)
Contusion | 2 (2.5%) | 0
Dysmenorrhea | 2 (2.7%) | 0
Incision site pruritus | 2 (2.7%) | 0
Nasal congestion | 2 (2.5%) | 0
Pruritus generalized | 2 (2.5%) | 0
* Percentages adjusted to account for the different sizes of the pooled studies.

Less common adverse reactions (incidence less than 2% and more frequent than either bupivacaine HCl or vehicle placebo) following POSIMIR administration in shoulder surgical procedures were angina pectoris, blepharospasm, electrocardiogram T wave amplitude decreased, fatigue, osteoarthritis, procedural nausea, procedural pain, and pulmonary arterial hypertension.

Additional follow-up safety data consisting of shoulder MRI, physical examination of the shoulder, and assessments of wound healing were collected at 6 months in Study 1 and at 18 months in Study 2. There were no specific long-term follow-up evaluations for patients treated in Study 3; however, study investigators did not report any cases of chondrolysis in follow-up surveys. All surgical incisions were found to have healed as expected in all three studies. Table 3 presents the results of the MRI and physical examinations for Study 1. Table 4 presents the results of the MRI and physical examinations for Study 2.

Table 3. 6-Month Follow-up Safety Data from Subacromial Decompression Study 1.
Safety Evaluation | Posimir | Vehicle Placebo | Bupivacaine HCl
Number enrolled | 53 | 25 | 29
Shoulder MRI
Number at 6-month follow-up | 51 | 25 | 25
Improved[1], n (%) | 6 (11.8%) | 2 (8.0%) | 6 (24.0%)
No change[1], n (%) | 31 (60.8%) | 14 (56.0%) | 9 (36.0%)
Worsened[1], n (%) | 14 (27.4%) | 9 (36%) | 10 (40%)
Constant-Murley score
Number at 6-month follow-up | 52 | 25 | 26
Pre-surgery, mean (SD) | 44.7 (12.5%) | 41.7 (11.7%) | 42 (11.3%)
Follow-up, mean (SD) | 61.6 (15.2%) | 63.2 (12.4%) | 65.6 (6.8%)
Decreased from baseline. n (%) | 5 (9.6%) | 2 (8.0%) | 0 (0%)
[1] Compared with pre-surgical MRI

Table 4. 18-Month Follow-up Safety Data from Subacromial Decompression Study 2.
Safety Evaluation | Posimir | Vehicle Placebo
Number enrolled | 40 | 20
Shoulder MRI
Number at 18-month follow-up | 27 | 14
Overall assessment
Unexpected injuries or findings compared with pre-surgical MRI, n (%) | 0 | 0
New-onset cartilage or bone lesions of concern (not present at baseline and unrelated to surgery or natural disease progression), n (%) | 0 | 0
Glenohumeral joint and humeral head
Presence of cartilage thinning - humeral head, n (%)
Grade 0: normal/none | 26 (96.3%) | 14 (100%)
Grade 1: mild | 0 | 0
Grade 2: moderate | 1 (3.7%)[1] | 0
Grade 3: severe | 0 | 0
Rotator cuff and labrum
Supraspinatus tendon tear, n (%)
No tear | 16 (59.3%) | 5 (35.7%)
Partial | 7 (25.9%) | 7 (50.0%)
Full thickness | 1 (3.7%) | 0
Other findings | 3 (11.1%) | 2 (14.3%)
Supraspinatus - other findings, n (%)
Interstitial tear | 0 | 0
Tendinosis | 2 (7.4%) | 1 (7.1%)
Surgically repaired tendon | 0 | 1 (7.1%)
Interstitial tear/tendinosis | 1 (3.7%) | 0
(blank) | 24 (88.9%) | 12 (85.7%)
Subacromial space - acromion
Acromion bony spur, n (%)
Yes | 1 (3.7%) | 0
No | 26 (96.3%) | 14 (100%)
Acromion bone resection, n (%)
Yes | 18 (66.7%) | 9 (64.3%)
No | 9 (33.3%) | 5 (35.7%)
Acromion signal abnormality (edema, fibrosis), n (%)
Yes | 2 (7.4%)[2] | 2 (14.3%)[2]
No | 25 (92.6%)[2] | 12 (85.7%)[2]
Acromioclavicular joint
Bone resection at acromioclavicular joint/postoperative changes, n (%)
Yes | 10 (37.0%) | 4 (28.6%)
No | 16 (59.3%) | 10 (71.4%)
Not evaluable | 1 (3.7%) | 0
Joint effusion/synovitis, n (%)
Grade 0: normal/none | 9 (33.3%) | 2 (14.3%)
Grade 1: mild | 9 (33.3%)[3] | 7 (50.0%)
Grade 2: moderate | 3 (11.1%)[3] | 3 (21.4%)[3]
Grade 3: severe | 0 | 1 (7.1%)[3]
Not evaluable | 6 (22.2%) | 1 (7.1%)
Bursa and Soft Tissue
Subacromial bursa - bursitis/excess fluid, n (%)
Grade 0: normal/none | 18 (66.7%) | 5 (35.7%)
Grade 1: mild | 6 (22.2%) | 9 (64.3%)[4]
Grade 2: moderate | 3 (11.1%) | 0
Grade 3: severe | 0 | 0
Physical Exam
Number at 18-month follow-up | 31 | 16
Clinical assessment, n (%)
Normal | 27 (87.1%) | 13 (81.3%)
Abnormal | 4 (12.9%) | 3 (18.8%)
Pain intensity, 0-10 scale
Mean (SE) | 0.9 (0.4%) | 1.2 (0.6%)
Positive impingement sign, n (%)
Yes | 3 (9.7%) | 3 (18.8%)
No | 28 (90.3%) | 13 (81.3%)
Full passive range of motion, n (%)
Yes | 27 (87.1%) | 13 (81.3%)
No | 4 (12.9%) | 3 (18.8%)
[1] The humeral head cartilage thinning was unchanged from baseline.
[2] Two POSIMIR patients were positive for signal abnormalities at baseline and negative at 18 months. Two POSIMIR patients were negative for signal abnormalities at baseline and positive at 18 months. One placebo patient was positive for signal abnormality at baseline and negative at 18 months. Two placebo patients were positive for signal abnormalities at both baseline and 18 months.
[3] Two POSIMIR patients had joint effusion/synovitis that improved from moderate at baseline to mild at 18 months.
One POSIMIR patient had joint effusion/synovitis that improved from severe at baseline to mild at 18 months. Four patients (1 POSIMIR, 3 placebo) had joint effusion/synovitis that worsened from mild at baseline to moderate at 18 months. One placebo patient had joint effusion/synovitis that worsened from mild at baseline to severe at 18 months.
[4] One placebo patient had bursitis/excess fluid that was severe at baseline and mild at 18 months.

Soft tissue surgical procedures

There were two studies evaluating the safety of POSIMIR in patients undergoing inguinal hernia repair (hernioplasty). Patients in these studies were administered either POSIMIR 5 mL or vehicle placebo; 2.5 mL administered into the floor of the inguinal canal and 2.5 mL administered into the subcutaneous space. Table 5 presents commonly-reported adverse reactions from these studies.

Table 5. Commonly Reported Adverse Reactions Pooled from Studies in Inguinal Hernia Repair (Incidence ≥ 2% and More Frequent than Placebo)
Preferred Term, n (%)* | Posimir (N=69) | Vehicle Placebo (N=53)
Bradycardia | 16 (22.9%) | 7 (14.2%)
Pruritus† | 15 (21.6%) | 9 (17.5%)
Post procedural contusion (bruising) | 10 (14.0%) | 5 (10.1%)
Vomiting | 6 (9.4%) | 4 (7.4%)
Incision site swelling | 4 (6.0%) | 3 (5.7%)
Dyspepsia | 4 (5.7%) | 2 (3.7%)
Pyrexia | 4 (6.0%) | 2 (4.0%)
Contusion | 4 (5.7%) | 0
Back pain | 3 (4.1%) | 2 (3.4%)
Viral infection | 3 (4.1%) | 2 (4.0%)
Incision site erythema | 3 (4.1%) | 0
Oropharyngeal pain | 3 (4.6%) | 0
Tachycardia | 3 (4.6%) | 0
Upper respiratory tract infection | 2 (3.0%) | 1 (2.0%)
Dry throat | 2 (3.2%) | 0
Hyperhidrosis | 2 (3.0%) | 0
Hypertension | 2 (2.8%) | 0
Local swelling | 2 (3.0%) | 0
Testicular swelling | 2 (3.2%) | 0
* Percentages adjusted to account for the different sizes of the pooled studies.
† Incision site pruritus, generalized pruritus, and genital pruritus were also reported, but none had incidence ≥2% and more frequent than placebo.

There were five studies evaluating the safety of POSIMIR in laparoscopic, laparoscopically-assisted, or open abdominal surgeries.

In two studies in patients undergoing laparoscopic cholecystectomy, POSIMIR or bupivacaine HCl was administered into the laparoscopic port incisions at the end of surgery. In one of these studies, a subset of patients received either POSIMIR or saline placebo. In a study of patients undergoing laparoscopically-assisted colectomy, POSIMIR or vehicle placebo was administered predominantly into the hand port incision at the end of surgery. In a study of patients undergoing laparotomy, POSIMIR or bupivacaine HCl was administered into the full length of the surgical incision at the end of surgery. Table 6 presents commonly-reported adverse reactions from these four studies. Table 7 and Table 8 present, respectively, surgical-site adverse reactions and early-occurring central nervous system (CNS)-related adverse reactions from the laparoscopic cholecystectomy study that included a saline placebo control arm.

Table 6. Commonly Reported Adverse Reactions Pooled from Laparoscopic, Laparoscopically-Assisted, and Open Abdominal Surgery Studies (Incidence ≥ 2% and More Frequent than Bupivacaine HCl or Placebo).
Preferred Term, n (%)* | Posimir (N=337) | Bupivacaine HCl (N=186) | Vehicle Placebo (N=78)
Post procedural contusion (bruising) | 231 (71.2%) | 119 (61.8%) | 41 (52.6%)
Nausea | 189 (55.8%) | 111 (59.6%) | 40 (51.3%)
Constipation | 112 (35.2%) | 80 (41.8%) | 8 (10.3%)
Somnolence | 92 (30.4%) | 80 (41.0%) | 3 (3.8%)
Headache | 86 (27.2%) | 63 (32.3%) | 12 (15.4%)
Dizziness | 75 (23.5%) | 58 (30.1%) | 6 (7.7%)
Vomiting | 66 (19.4%) | 39 (21.0%) | 6 (7.7%)
Dysgeusia | 50 (16.2%) | 33 (16.9%) | 2 (2.6%)
Pruritus† | 45 (14.3%) | 36 (18.7%) | 5 (6.4%)
Procedural pain | 35 (11.4%) | 35 (17.8%) | 0
Diarrhea | 34 (9.8%) | 10 (5.5%) | 10 (12.8%)
Incision site hemorrhage | 30 (8.7%) | 6 (3.0%) | 3 (3.8%)
Pyrexia | 29 (8.2%) | 10 (5.7%) | 11 (14.1%)
Abdominal distension | 29 (8.2%) | 8 (4.8%) | 12 (15.4%)
Incision site erythema | 29 (8.1%) | 5 (2.7%) | 10 (12.8%)
Post procedural discharge | 26 (7.5%) | 8 (4.4%) | 7 (9.0%)
Paresthesia | 23 (7.5%) | 25 (13.1%) | 2 (2.6%)
Hypokalemia | 22 (5.9%) | 2 (1.4%) | 10 (12.8%)
Incision site hematoma | 18 (5.2%) | 3 (1.7%) | 4 (5.1%)
Anemia | 17 (4.5%) | 1 (0.7%) | 7 (9.0%)
Flatulence | 16 (4.6%) | 7 (4.0%) | 8 (10.3%)
Hypertension | 16 (4.6%) | 7 (3.6%) | 1 (1.3%)
Incision site infection | 16 (4.5%) | 4 (2.5%) | 2 (2.6%)
Musculoskeletal pain | 15 (4.2%) | 8 (4.9%) | 0
Abdominal pain | 15 (4.4%) | 1 (0.5%) | 1 (1.3%)
Insomnia | 14 (3.9%) | 5 (2.9%) | 7 (9.0%)
Dyspepsia | 13 (3.8%) | 3 (1.9%) | 4 (5.1%)
Wound dehiscence | 13 (3.6%) | 3 (1.5%) | 5 (6.4%)
Cough | 12 (3.6%) | 3 (1.8%) | 1 (1.3%)
Oropharyngeal pain | 12 (3.5%) | 2 (1.0%) | 0
Urinary retention | 10 (2.8%) | 2 (1.2%) | 4 (5.1%)
Chest pain | 10 (2.9%) | 1 (0.5%) | 1 (1.3%)
Ileus | 10 (2.7%) | 1 (0.7%) | 3 (3.8%)
Body temperature increased | 9 (2.4%) | 0 | 2 (2.6%)
Abdominal pain upper | 8 (2.5%) | 2 (1.0%) | 0
Rash | 7 (2.1%) | 7 (3.8%) | 1 (1.3%)
Pain in extremity | 7 (2.1%) | 5 (2.8%) | 1 (1.3%)
Dry mouth | 7 (2.2%) | 2 (1.0%) | 1 (1.3%)
Nasopharyngitis | 7 (2.1%) | 0 | 0
* Percentages adjusted to account for the different sizes of the pooled studies.
† Incision site pruritus, generalized pruritus, eye pruritus, anal pruritus, and infusion site pruritus were also reported, but none had incidence ≥2% and more frequent than placebo.

Table 7. Incidence of Surgical Site Adverse Reactions from Laparoscopic Cholecystectomy Study with Saline Placebo and Bupivacaine HCl Controls.
 | Saline Placebo Control |  | Bupivacaine HCl Control
Prespecified Term*, n (%) | Posimir (N=45) | Saline Placebo (N=47) | Posimir (N=148) | Bupivacaine HCl (N=148)
Visible bruising | 41 (91.1%) | 33 (70.2%) | 142 (95.9%) | 105 (70.9%)
Surgical site bleeding | 22 (48.9%) | 20 (42.6%) | 19 (12.8%) | 24 (16.2%)
Drainage from surgical incision(s) | 2 (4.4%) | 3 (6.4%) | 11 (7.4%) | 6 (4.1%)
Wound hematoma | 0 | 0 | 6 (4.1%) | 2 (1.4%)
Wound dehiscence | 0 | 0 | 2 (1.4%) | 3 (2.0%)
Surgical site infection | 0 | 0 | 2 (1.4%) | 1 (0.7%)
* Terms were prespecified for examination by a blinded assessor on postoperative days 0, 4, 7, 14, 28, and 59.

Table 8. CNS-related Adverse Reactions Solicited from Subjects at 6 Hours Post-surgery in Laparoscopic Cholecystectomy Study with Saline Placebo and Bupivacaine HCl Controls.
 | Saline Placebo Control |  | Bupivacaine HCl Control
Dictionary-Derived Term (Symptom)* | Posimir (N=45) | Saline Placebo (N=47) | Posimir (N=148) | Bupivacaine HCl (N=148)
Entire study, n (%)
Somnolence (Drowsiness) | 18 (40.0%) | 16 (34.0%) | 60 (40.5%) | 48 (32.4%)
Nausea (Nausea) | 9 (20.0%) | 13 (27.7%) | 48 (32.4%) | 57 (38.5%)
Dizziness (Dizziness) | 3 (6.7%) | 3 (6.4%) | 28 (18.9%) | 31 (20.9%)
Headache (Headache) | 5 (11.1%) | 4 (8.5%) | 23 (15.5%) | 18 (12.2%)
Vomiting (Vomiting) | 2 (4.4%) | 3 (6.4%) | 10 (6.8%) | 15 (10.1%)
Constipation (Constipation) | 0 (0.0%) | 4 (8.5%) | 9 (6.1%) | 10 (6.8%)
Pruritus (Itching) | 1 (2.2%) | 1 (2.1%) | 6 (4.1%) | 5 (3.4%)
Subset of study, n (%) | N=23 | N=22
Dysgeusia (Metallic taste in mouth) | 3 (13.0%) | 2 (9.1%) | 26 (17.6%) | 22 (14.9%)
Paresthesia (Tingling) | 0 | 0 | 2 (1.4%) | 6 (4.1%)
Hypoesthesia (Numbness) | 0 | 0 | 1 (0.7%) | 1 (0.7%)
* Patients responded to a 10-symptom checklist (7 symptoms for part of the saline placebo-controlled portion of the study).

In a study of patients undergoing total abdominal hysterectomy, POSIMIR, vehicle placebo, or bupivacaine HCl was administered into the surgical incision at the end of surgery. Table 9 presents commonly-reported adverse reactions from this study.

Table 9. Commonly Reported Adverse Reactions from Total Abdominal Hysterectomy Study (Incidence ≥ 2% and More Frequent than Bupivacaine HCl).
Preferred Term | Posimir (N=60) | Bupivacaine HCl (N=27) | Vehicle Placebo (N=27)
Post procedural contusion (bruising) | 36 (60.0%) | 0 | 9 (33.3%)
Anemia | 10 (16.7%) | 3 (11.1%) | 4 (14.8%)
Dizziness | 9 (15.0%) | 4 (14.8%) | 3 (11.1%)
Vomiting | 9 (15.0%) | 4 (14.8%) | 8 (29.6%)
C-reactive protein increased | 7 (11.7%) | 1 (3.7%) | 0
Pyrexia | 7 (11.7%) | 7 (25.9%) | 3 (11.1%)
Somnolence | 5 (8.3%) | 2 (7.4%) | 0
Blood potassium decreased | 4 (6.7%) | 0 | 1 (3.7%)
Hypertension | 4 (6.7%) | 2 (7.4%) | 1 (3.7%)
Incision site hematoma | 3 (5.0%) | 0 | 0
Electrocardiogram change | 2 (3.3%) | 0 | 0
Procedural hemorrhage | 2 (3.3%) | 0 | 0
Vaginal hematoma | 2 (3.3%) | 0 | 0

Less common adverse reactions (incidence less than 2% and more frequent than either bupivacaine HCl or placebo) following POSIMIR administration in soft tissue surgical procedures were: application site irritation, atrial fibrillation, drug eruption, electrocardiogram QT prolonged, eructation, erythema, excessive granulation tissue, fatigue, genital pain, heart rate increased, hiccups, hypoesthesia, hypogeusia, incision site cellulitis, incision site erosion, incision site hypoesthesia, incision site inflammation, incision site edema, incision site pain, incision site rash, mean arterial pressure increased, micturition urgency, night sweats, overdose, palpitations, procedural hypertension, pruritus generalized, rash generalized, seroma, sinus tachycardia, skin discoloration, tinnitus, and wound hemorrhage.

7 DRUG INTERACTIONS

Do not dilute or mix POSIMIR with local anesthetics or other drugs or diluents.

Avoid additional use of local anesthetics within 168 hours following administration of POSIMIR.

7.1 Drugs Associated with Methemoglobinemia

Patients who are administered POSIMIR are at increased risk of developing methemoglobinemia when concurrently exposed to following drugs, which could include other local anesthetics [see Warnings and Precautions (5.4)].

Examples of Drugs Associated with Methemoglobinemia:

Class | Examples
Nitrates/Nitrites | nitric oxide, nitroglycerin, nitroprusside, nitrous oxide
Local anesthetics | articaine, benzocaine, bupivacaine, lidocaine, mepivacaine, prilocaine, procaine, ropivacaine, tetracaine
Antineoplastic agents | cyclophosphamide, flutamide, hydroxyurea, ifosfamide, rasburicase
Antibiotics | dapsone, nitrofurantoin, para-aminosalicylic acid, sulfonamides
Antimalarials | chloroquine, primaquine
Anticonvulsants | phenobarbital, phenytoin, sodium valproate
Other drugs | acetaminophen, metoclopramide, quinine, sulfasalazine

8 USE IN SPECIFIC POPULATIONS

8.1 Pregnancy

Risk Summary

There are no studies conducted with POSIMIR in pregnant women. In animal studies, embryo-fetal lethality was noted when bupivacaine was administered subcutaneously to pregnant rabbits during organogenesis at 0.6 times the maximum recommended human dose of POSIMIR at 660 mg bupivacaine. Decreased pup survival was observed in a rat pre- and post-natal development study (dosing from implantation through weaning) at 0.6 times the maximum recommended human dose of POSIMIR at 660 mg bupivacaine. Based on animal data, advise pregnant women of the potential risks to a fetus. [see Data]

The background risk of major birth defects and miscarriage for the indicated population is unknown. However, the background risk in the U.S. general population of major birth defects is 2%-4% and of miscarriage is 15%-20% of clinically recognized pregnancies.

Clinical Considerations

Labor or Delivery

Bupivacaine is contraindicated for obstetrical paracervical block anesthesia. While POSIMIR has not been studied with this technique, the use of bupivacaine for obstetrical paracervical block anesthesia has resulted in fetal bradycardia and death. Bupivacaine can rapidly cross the placenta, and when used for epidural, caudal, or pudendal block anesthesia, can cause varying degrees of maternal, fetal, and neonatal toxicity (POSIMIR is not indicated for these uses). The incidence and degree of toxicity depend upon the procedure performed, the type, and amount of drug used, and the technique of drug administration. Adverse reactions in the parturient, fetus, and neonate involve alterations of the central nervous system, peripheral vascular tone, and cardiac function.

Data

Animal Data

Bupivacaine hydrochloride produced developmental toxicity when administered subcutaneously to pregnant rats and rabbits at clinically relevant doses.

Bupivacaine hydrochloride was administered subcutaneously to rats at doses of 4.4, 13.3, & 40 mg/kg and to rabbits at doses of 1.3, 5.8, & 22.2 mg/kg during the period of organogenesis (implantation to closure of the hard palate). The high doses are approximately 0.6 times the daily maximum recommended human dose (MRHD) of 660 mg/day on a mg/m^2 body surface area (BSA) basis. No embryo-fetal effects were observed in rats at the high dose which caused increased maternal lethality. An increase in embryo-fetal deaths was observed in rabbits at the high dose in the absence of maternal toxicity with the fetal No Observed Adverse Effect Level representing approximately 0.2 times the MRHD on a BSA basis.

In a rat pre- and post-natal developmental study (dosing from implantation through weaning) conducted at subcutaneous doses of 4.4, 13.3, & 40 mg/kg, decreased pup survival was observed at the high dose. The high dose is approximately 0.6 times the daily MRHD of 660 mg/day on a BSA basis.

8.2 Lactation

Risk Summary

POSIMIR has not been studied in nursing mothers. Bupivacaine can persist in plasma for up to 168 hours [see Clinical Pharmacology (12) ] and benzyl alcohol, a POSIMIR excipient, for up to 12 hours after POSIMIR administration. Both bupivacaine and benzyl alcohol have been reported to be excreted in human milk. The developmental and health benefits of breastfeeding should be considered along with the mother's clinical need for POSIMIR and any potential adverse effects on the breastfed infant from POSIMIR or from the underlying maternal condition.

8.4 Pediatric Use

Safety and effectiveness of POSIMIR in pediatric patients below the age of 18 have not been established.

8.5 Geriatric Use

Of the total number of patients enrolled in the POSIMIR clinical studies (N=1463), 167 patients were older than 65 years and 32 patients were older than 75 years.

In bupivacaine clinical studies, differences in various pharmacokinetic parameters have been observed between elderly and younger adult patients. Bupivacaine is known to be substantially excreted by the kidney, and the risk of adverse reactions to bupivacaine may be greater in patients with impaired renal function. Because elderly patients are more likely to have decreased renal function, care should be taken in dose selection, and it may be useful to monitor renal function. Elderly patients may require lower doses of POSIMIR. Consider increased monitoring for local anesthetic systemic toxicity when administering POSIMIR to elderly patients.

8.6 Hepatic Impairment

Because amide-type local anesthetics, such as bupivacaine, are metabolized by the liver, these drugs should be used with caution in patients with hepatic impairment. Patients with severe hepatic impairment, because of their inability to metabolize local anesthetics normally, are at a greater risk of developing toxic plasma concentrations, and potentially local anesthetic systemic toxicity. Care should be taken when considering the use of POSIMIR in patients with impaired hepatic function and consider reduced dosing. Consider increased monitoring for local anesthetic systemic toxicity in patients with moderate to severe hepatic impairment when administering POSIMIR.

8.7 Renal Impairment

Bupivacaine is known to be substantially excreted by the kidney, and the risk of adverse reactions to this drug may be greater in patients with impaired renal function. Care should be taken when considering the use of POSIMIR in patients with impaired renal function. Consider increased monitoring for local anesthetic systemic toxicity when administering POSIMIR to patients with impaired renal function.

10 OVERDOSAGE

Acute emergencies from local anesthetics are generally related to high plasma concentrations encountered during therapeutic use of local anesthetics or to unintended intravascular injection of local anesthetic solution [see Warnings and Precautions (5)].

In the clinical study program, a maximum plasma concentration (Cmax) of 2850 ng/mL was reported. No apparent bupivacaine-related adverse reactions or clinical sequelae were observed in patients with high bupivacaine plasma concentrations.

11 DESCRIPTION

POSIMIR (bupivacaine solution) is a sterile nonpyrogenic, clear, light yellow to amber solution for infiltration. Over time, the solution color will intensify within the range, from light yellow to amber. The range of color is not associated with a change in potency of the drug product. POSIMIR contains bupivacaine (132 mg/mL), benzyl alcohol, and sucrose acetate isobutyrate.

Bupivacaine, an amide-type local anesthetic, is 1-butyl-N-(2,6-dimethylphenyl)-2-piperidinecarboxamide. It is a white crystalline powder with a molecular weight of 288.43 g/mol. The structure of bupivacaine is shown below:

Bupivacaine is present in POSIMIR at a concentration of 132 mg/mL.

12 CLINICAL PHARMACOLOGY

12.1 Mechanism of Action

Bupivacaine blocks the generation and the conduction of nerve impulses, presumably by increasing the threshold for electrical excitation in the nerve, by slowing the propagation of the nerve impulse, and by reducing the rate of rise of the action potential. In general, the progression of anesthesia is related to the diameter, myelination and conduction velocity of affected nerve fibers. Clinically, the order of loss of nerve function is as follows: (1) pain, (2) temperature, (3) touch, (4) proprioception, and (5) skeletal muscle tone.

12.2 Pharmacodynamics

Systemic absorption of bupivacaine produces effects on the cardiovascular and central nervous systems. At blood concentrations achieved with therapeutic doses, changes in cardiac conduction, excitability, refractoriness, contractility, and peripheral vascular resistance are minimal. However, toxic blood concentrations depress cardiac conduction and excitability, which may lead to atrioventricular block, ventricular arrhythmias and to cardiac arrest, sometimes resulting in fatalities. In addition, myocardial contractility is depressed and peripheral vasodilation occurs, leading to decreased cardiac output and arterial blood pressure. These cardiovascular changes are more likely to occur after unintended intravascular injection of liquid formulations of bupivacaine.

Following systemic absorption, local anesthetics can produce central nervous system stimulation, depression or both. Apparent central stimulation is usually manifested as restlessness, tremors and shivering, progressing to convulsions, followed by depression and coma, progressing ultimately to respiratory arrest. However, the local anesthetics have a primary depressant effect on the medulla and on higher centers. The depressed stage may occur without a prior excited stage.

12.3 Pharmacokinetics

Infiltration of POSIMIR into the surgical wound results in plasma levels of bupivacaine that can persist for 168 hours. Systemic plasma levels of bupivacaine following administration of POSIMIR are not correlated with local efficacy.

Absorption

The rate of systemic absorption of bupivacaine is dependent upon the total dose of drug administered, the route of administration, and the vascularity of the administration site.

Pharmacokinetic parameters of bupivacaine are shown in Table 10 after single-dose infiltration of POSIMIR in arthroscopic subacromial decompression surgical procedure.

Table 10. Summary of Pharmacokinetic Parameters for Bupivacaine after Administration of a Single Dose of POSIMIR 5 mL (660 mg)
Surgical Procedure |  | Cmax (ng/mL) | AUC0-t# (h·ng/mL) | Tmax (h)^ | T1/2 (h)
Arthroscopic subacromial decompression Study 1* | N | 36 | 36 | 36 | 36
Arthroscopic subacromial decompression Study 1* | Mean | 593 | 19395 | 5.9^ | 16.4
Arthroscopic subacromial decompression Study 1* | SD | 299 | 12056 | 1.0-24.0^ | 5.1
Arthroscopic subacromial decompression Study 3 | N | 18 | 18 | 18 | 18
Arthroscopic subacromial decompression Study 3 | Mean | 1006 | 47015 | 8.0^ | 26.1
Arthroscopic subacromial decompression Study 3 | SD | 454 | 20040 | 2.1-26.9^ | 8.2
#t = last sampling time
^Median / Range (min-max)
* Drug leakage from the surgical site was suspected.

Distribution

Depending upon the route of administration, bupivacaine is distributed to some extent to all body tissues, with high concentrations found in highly perfused organs such as the liver, lungs, heart, and brain.

Bupivacaine appears to cross the placenta by passive diffusion. The rate and degree of diffusion is governed by (1) the degree of plasma protein binding, (2) the degree of ionization, and (3) the degree of lipid solubility. Fetal/maternal ratios of local anesthetics appear to be inversely related to the degree of plasma protein binding, because only the free, unbound drug is available for placental transfer. Bupivacaine with a high protein binding capacity (95%) has a low fetal/maternal ratio (0.2 to 0.4). The extent of placental transfer is also determined by the degree of ionization and lipid solubility of the drug. Lipid soluble, non-ionized drugs such as bupivacaine readily enter the fetal blood from the maternal circulation.

Elimination

The mean half-life of bupivacaine after POSIMIR administration in adults who underwent arthroscopic subacromial decompression range from 16.4 to 26.1 hours.

Metabolism

Amide-type local anesthetics such as bupivacaine are metabolized primarily in the liver via conjugation with glucuronic acid. Pipecoloxylidine is the major metabolite of bupivacaine. The elimination of drug from tissue distribution depends largely upon the availability of binding sites in the circulation to carry it to the liver where it is metabolized.

Excretion

The kidney is the main excretory organ for most local anesthetics and their metabolites. Urinary excretion is affected by urinary perfusion and factors affecting urinary pH. Only 6% of bupivacaine is excreted unchanged in the urine.

Specific Populations

Hepatic Impairment

Pharmacokinetics of POSIMIR have not been evaluated in patients with hepatic impairment. [see Warnings and Precautions (5) and Use in Specific Populations (8.6) ].

Renal Impairment

Pharmacokinetics of POSIMIR have not been evaluated in patients with renal impairment. [see Use in Specific Populations (8.7) ].

Geriatric Patients

Pharmacokinetics of POSIMIR have not been evaluated in geriatric patients.

Elderly patients have exhibited higher peak plasma concentrations than younger patients following administration of bupivacaine HCl. The total plasma clearance was decreased in these patients [see Use in Specific Populations (8.5)].

13 NONCLINICAL TOXICOLOGY

13.1 Carcinogenesis, Mutagenesis, Impairment of Fertility

Carcinogenesis

Long-term studies in animals to evaluate the carcinogenic potential of bupivacaine hydrochloride have not been conducted.

Mutagenesis

Bupivacaine was negative in the in vitro bacterial reverse mutation assay (Ames assay), the in vitro chromosomal aberration assay (human peripheral blood lymphocytes), and the in vivo rat micronucleus assay.

Impairment of Fertility

The effect of bupivacaine on fertility has not been determined.

13.2 Animal Toxicology and/or Pharmacology

Necrosis of the joint cartilage was observed following intra-articular injection of a single dose of POSIMIR or POSIMIR vehicle in the dog model.

14 CLINICAL STUDIES

The effectiveness of POSIMIR was evaluated in ten adequate and well-controlled studies in patients undergoing open and laparoscopic abdominal procedures, abdominal hysterectomy, inguinal hernia repair, and open and arthroscopic shoulder procedures. Adequate evidence of effectiveness was demonstrated in one of three studies conducted in patients undergoing shoulder surgery (described in detail below) and was not demonstrated in any soft tissue procedure evaluated.

Study 1

Study 1 was a randomized, multicenter, assessor blinded, placebo-controlled (vehicle) clinical trial in 107 patients undergoing arthroscopic subacromial decompression surgery with an intact rotator cuff. Associated procedures included inspection of the glenohumeral joint, distal clavicle excision, bursectomy, synovectomy, removal of loose body, resection of coracoacromial ligament and subacromial spurs, rotator cuff debridement, and minor debridement of articular cartilage. There were no open surgical procedures performed during this study. The mean age was 50 years (range 21 to 70 years), 60% of treated patients were female, 96% were White, 2% were Hispanic, 1% were Asian, and 1% were Other.

Patients were randomized 2:1:1 to receive POSIMIR, vehicle placebo, or bupivacaine HCl 50 mg, and all patients received general anesthesia. No analgesic pre-medication or local anesthetics were administered. POSIMIR and vehicle placebo were administered under direct arthroscopic visualization as single injections into the subacromial space through one of the arthroscopic portals at the end of the surgery. Bupivacaine HCl 50 mg was administered subacromially as a single dose. Post-operatively, patients received acetaminophen 500 mg or 1000 mg every six hours, depending on body weight, through 72 hours, and were allowed morphine rescue medication as needed, either 2 mg IV or 10 mg orally. Pain intensity was rated by the patients using a 0 to 10 numerical rating scale (NRS) at multiple time points up to 72 hours.

The primary outcome measures were the normalized area under the curve (nAUC) of mean pain intensity on movement scores collected at specified intervals over the first 72 hours after surgery and total opioid rescue analgesia (IV morphine-equivalent dose) through 72 hours. In this clinical study, POSIMIR 5 mL demonstrated a significant reduction in mean pain intensity compared with placebo of 1.3 points on a 0 to 10 NRS scale over 72 hours (Figure 1).

Figure 1. Mean Pain Intensity on Movement Through 72 Hours After Surgery,
Subacromial Decompression Study 1

The median total use of opioid rescue analgesia (IV morphine equivalent dose) from 0 to 72 hours for the POSIMIR treatment group (4 mg) was statistically lower than for the placebo treatment group (12 mg). The median use of opioid rescue analgesia in the bupivacaine treatment group was 8 mg.

Study 2

Study 2 was a randomized, double-blind, placebo-controlled (vehicle) clinical trial in 60 patients undergoing arthroscopic subacromial decompression, inspection of glenohumeral joint, synovectomy, removal of loose body, minor debridement of articular cartilage, minor debridement or minor repair of rotator cuff, open distal clavicle excision, bursectomy, and resection of coracoacromial ligament and subacromial spurs. The mean age was 48 years (range 27 to 68 years), 55% of treated patients were female, 95% were White, 2% were Asian, and 2% were Other.

Patients were randomized 2:1 to receive POSIMIR or vehicle placebo, and all patients received general anesthesia. Post-operatively, patients were allowed morphine rescue medication as needed, either 3 mg IV or 10 mg to 15 mg orally, or acetaminophen. Pain intensity was rated by the patients using a 0 to 10 numerical rating scale (NRS) at multiple time points up to 72 hours.

The primary outcome measures were mean pain intensity on movement AUC through 72 hours and total opioid rescue analgesia (IV morphine-equivalent dose) through 72 hours. There was no statistically significant difference in either primary endpoint between the POSIMIR and vehicle placebo treatment groups (Figure 2).

Figure 2: Mean Pain Intensity on Movement Through 72 Hours After Surgery,
Subacromial Decompression Study 2

Study 3

Study 3 was a randomized, double-blind, placebo-controlled (vehicle) and open-label PK clinical trial in 92 patients undergoing a variety of shoulder surgical procedures, including rotator cuff repair, subacromial decompression, glenoid labrum repair or debridement, and biceps tendon repair. The majority of patients underwent arthroscopic procedures; however, six patients underwent a combination of arthroscopic and open procedures. The mean age was 54 years (range 20 to 82 years), 59% of treated patients were male, 87% were White, 8% were African American, 3% were Other, and 2% were Asian.

An equal number of patients were randomized to two cohorts. The routes of POSIMIR or vehicle placebo administration in Cohort 1 were subacromial or subcutaneous injection or a combination. In Cohort 2, POSIMIR or vehicle placebo was administered via injection under direct arthroscopic visualization into the subacromial space. Surgical procedures were completed either under local or general anesthesia. Post-operatively, patients were allowed morphine IV, oxycodone orally, or acetaminophen orally as needed.

The primary outcome measures were mean pain intensity on movement and at rest through 120 hours and pain control through day seven. There was no statistically significant difference in either primary endpoint between POSIMIR and vehicle placebo treatment groups (Figure 3).

Figure 3: Mean Pain Intensity on Movement Through 120 Hours After Surgery,
Subacromial Decompression Study 3

16 HOW SUPPLIED/STORAGE AND HANDLING

POSIMIR (bupivacaine solution) is available in single‑dose vials. It is a sterile nonpyrogenic, clear, light yellow to amber solution in glass vials.

5 mL single-dose vial, 660 mg/5 mL (132 mg/mL) packaged in a 10-unit carton
(NDC 51715-660-10)

Storage

POSIMIR vial should be stored at a controlled room temperature of 20°C to 25°C (68°F to 77°F), excursions permitted to 15°C to 30°C (59°F to 86°F). [See USP Controlled Room Temperature]. Vial should be protected from light and retained in carton until time of use.

Handling

- Do not administer any solution which contains particulate matter.
- Do not autoclave.
- Do not dilute.
- Discard any unused portion in an appropriate manner.

NDC No. | Container | Size | Quantity
NDC 51715-660-10 | Single-dose vials | 5 mL | Box of 10

17 PATIENT COUNSELING INFORMATION

Patients should be informed in advance that bupivacaine-containing products can cause temporary loss of sensation or motor activity in the area of infiltration. The physician should discuss other information including adverse reactions in the POSIMIR package insert with their patients.

Distributed by Innocoll Pharmaceuticals Limited, Athlone, Ireland N37 VW42
This product and its use are covered by US Patent Nos. 8,153,149, 8,153,661, 8,753,665, 8,846,072 and other patents pending.

Revised: 02/2022

Principal Display Panel - 5 mL Carton Label

5 mL vial x 10 vials per carton

NDC 51715-660-10

Rx Only

Posimir®

(bupivacaine solution)

660 mg/5 mL
(132 mg/mL)

FOR INFILTRATION

Not for any other route of administration.

Do not dilute.

Principal Display Panel - 5 mL Vial Label

NDC 51715-660-10

Posimir®

(bupivacaine solution)

660 mg/5 mL
(132 mg/mL)

FOR INFILTRATION

Not for any other route of administration.

5 mL single dose vial

Discard unused portion. Do not dilute.